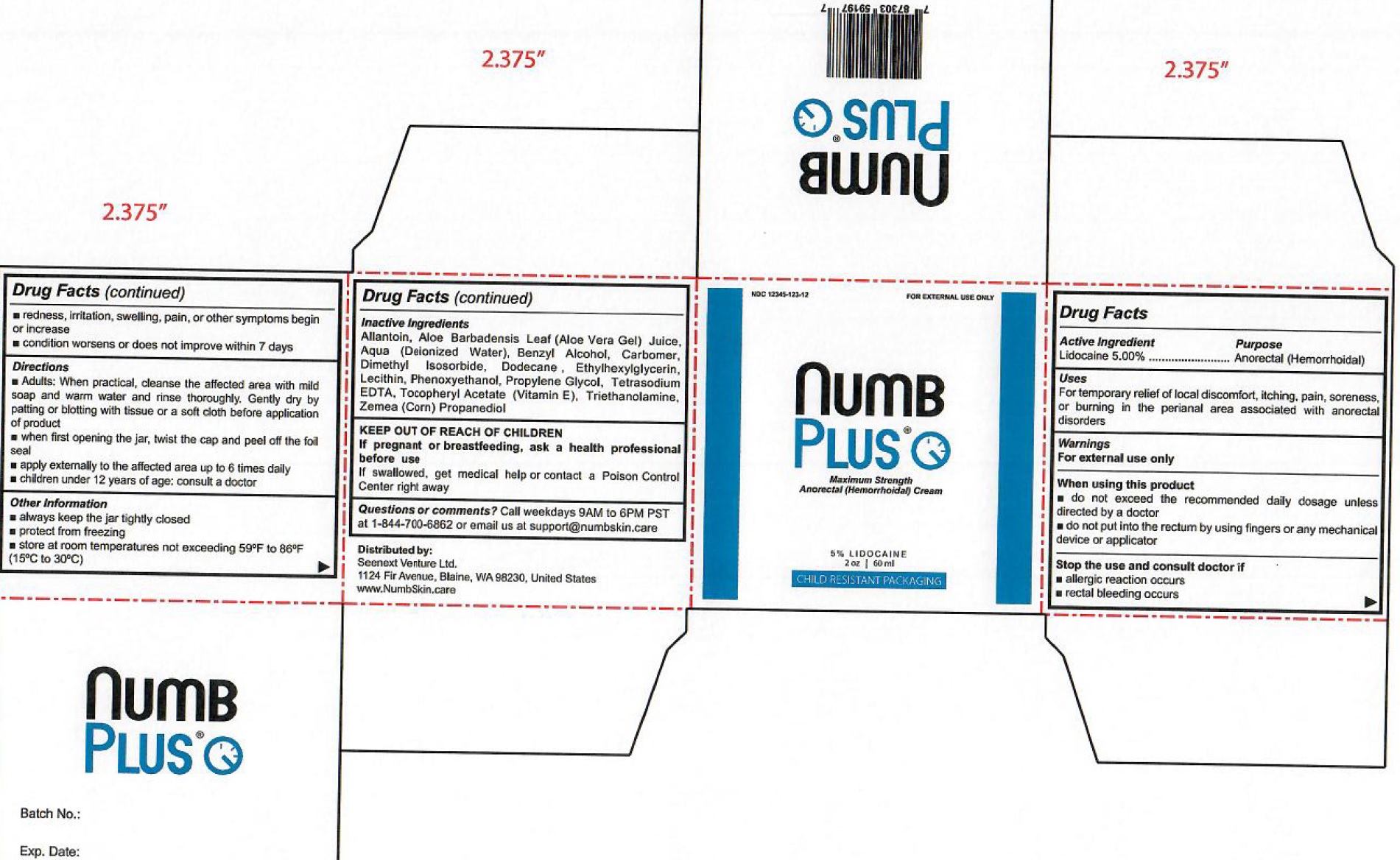 DRUG LABEL: NUMB PLUS Maximum Strength Anorectal
NDC: 70907-098 | Form: GEL
Manufacturer: SEENEXT VENTURE LTD
Category: otc | Type: HUMAN OTC DRUG LABEL
Date: 20231105

ACTIVE INGREDIENTS: LIDOCAINE 50 mg/1 mL
INACTIVE INGREDIENTS: ALLANTOIN; ALOE VERA LEAF; WATER; BENZYL ALCOHOL; CARBOMER HOMOPOLYMER, UNSPECIFIED TYPE; DIMETHYL ISOSORBIDE; DODECANE; ETHYLHEXYLGLYCERIN; PHENOXYETHANOL; PROPYLENE GLYCOL; EDETATE SODIUM; .ALPHA.-TOCOPHEROL; TROLAMINE; CORN; PROPANEDIOL

NUMB PLUS Maximum Strength Anorectal Cream

Active Ingredient

Lidocaine 5.00%

Purpose

Anorectal (Hermorrhoidal)

Uses

For temporary relief of local discomfort, itching, pain, soreness, or burning in the perianal area associated with anorectal disorders

Warnings

For external use only

When using this product

- do not exceed the recommended daily dosage unless directed by a doctor
- do not put into the rectum by using fingers or any mechanical device or applicator

Stop the use and consult doctor if

- allergic reaction occurs
- rectal bleeding occurs
- redness, irritation, swelling, pain, or other symptoms begin or increase
- condition worsens or does not improve within 7 days

KEEP OUT OF REACH OF CHILDREN

If swallowed, get medical help or contact a Poison Control Center right away

If pregnant or breastfeeding,

ask a health professional before use

Directions

- Adults: when practical, cleanse the affected area with mild soap and warm water and rinse thoroughly. Gently dry by patting or blotting with tissue or a soft cloth before application of product
- when first opening the jar, twist the cap and peel off the foil seal
- apply externally to the affected area up to 6 times daily
- children under 12 years of age: consult a doctor

Other Information

- always keep the jar tightly closed
- protect from freezing
- store at room temperatures not exceeding 59°F to 86°F (15°C to 30°C)

Inactive Ingredients

Allantoin, Aloe Barbadensis Leaf (Aloe Vera Gel) Juice, Aqua (Deionized Water), Benzyl Alcohol, Carbomer, Dimethyl Isosorbide, Dodecane, Ethylhexylglycerin, Lecithin, Phenoxyethanol, Propylene Glycol, Tetrasodium EDTA, Tocopheryl Acetate (Vitamin E), Triethanolamine, Zemea (Corn) Propanediol

Questions or comments?

Call weekdays 9AM to 6PM PST at 1-844-700-6862 or email us at Support@numbskin.care